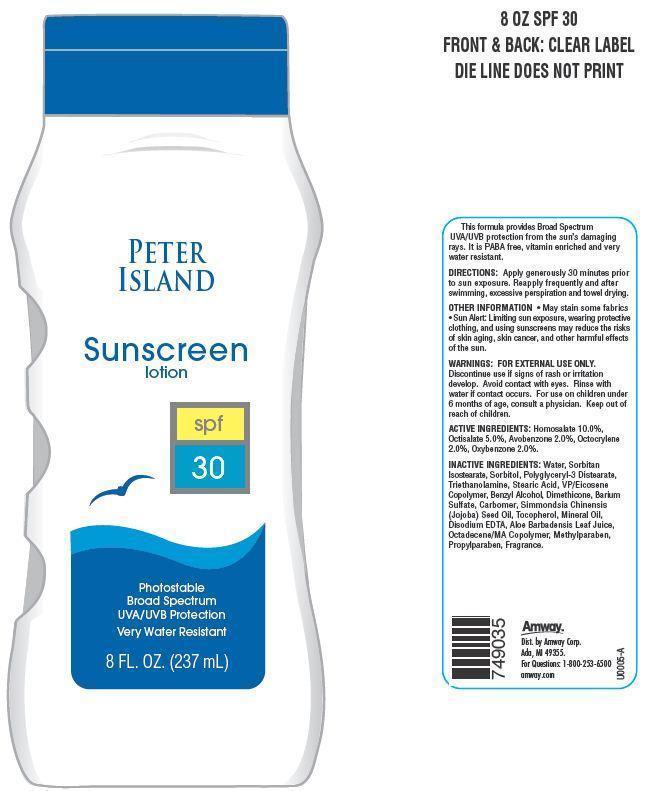 DRUG LABEL: Peter Island Sunscreen
NDC: 10056-705 | Form: LOTION
Manufacturer: Access Business Group LLC
Category: otc | Type: HUMAN OTC DRUG LABEL
Date: 20130628

ACTIVE INGREDIENTS: HOMOSALATE 10 g/100 g; OXYBENZONE 2 g/100 g; AVOBENZONE 2 g/100 g; OCTISALATE 5 g/100 g; OCTOCRYLENE 2 g/100 g
INACTIVE INGREDIENTS: WATER; SORBITAN ISOSTEARATE; SORBITOL; TROLAMINE; STEARIC ACID; BENZYL ALCOHOL; DIMETHICONE; BARIUM SULFATE; JOJOBA OIL; TOCOPHEROL; MINERAL OIL; EDETATE DISODIUM; ALOE VERA LEAF; METHYLPARABEN; PROPYLPARABEN

ACTIVE INGREDIENTS:

Homosalate 10.0%

Octisalate 5.0%

Avobenzone 2.0%

Octocrylene 2.0%

Oxybenzone 2.0%

WARNINGS:

FOR EXTERNAL USE ONLY.
Avoid contact with eyes. Rinse with water if contact occurs.

STOP USE

Discontinue use if signs of rash or irritation develop.

ASK DOCTOR

For use on children under the age of 6 months consult a physician.

Keep out of reach of children.

DIRECTIONS:

Apply generously and evenly 30 minutes before sun exposure. Reapply frequently and after swimming, excessive perspiration and towel drying.

OTHER INFORMATION

- May stain some fabrics
- Sun Alert: Limiting sun exposure, wearing protective clothing, and using sunscreens may reduce the risks of skin aging, skin cancer, and other harmful effects of the sun.

This formula provides Broad Spectrum UVA/UVB protection from the sun's damaging rays. It is PABA free, vitamin enriched and very water resistant.

Principal Display Panel

PETER ISLAND

Sunscreen lotion

spf 30

Photostable

Broad Spectrum

UVA/UVB Protection

Very Water Resistant

8 FL.OZ. (237 mL)

INACTIVE INGREDIENTS:

Water, Sorbitan Isostearate, Sorbitol, Polyglyceryl-3 Distearate, Triethanolamine, Stearic Acid, VP/Eicosene Copolymer, Benzyl Alcohol, Dimethicone, Barium Sulfate, Carbomer, Simmondsia Chinensis (jojoba) Seed Oil, Tocopherol, Mineral Oil, Disodium EDTA, Aloe Barbadensis Leaf Juice, Octadecene/MA Co polymer, MethylParaben, Propylparaben, Fragrance.